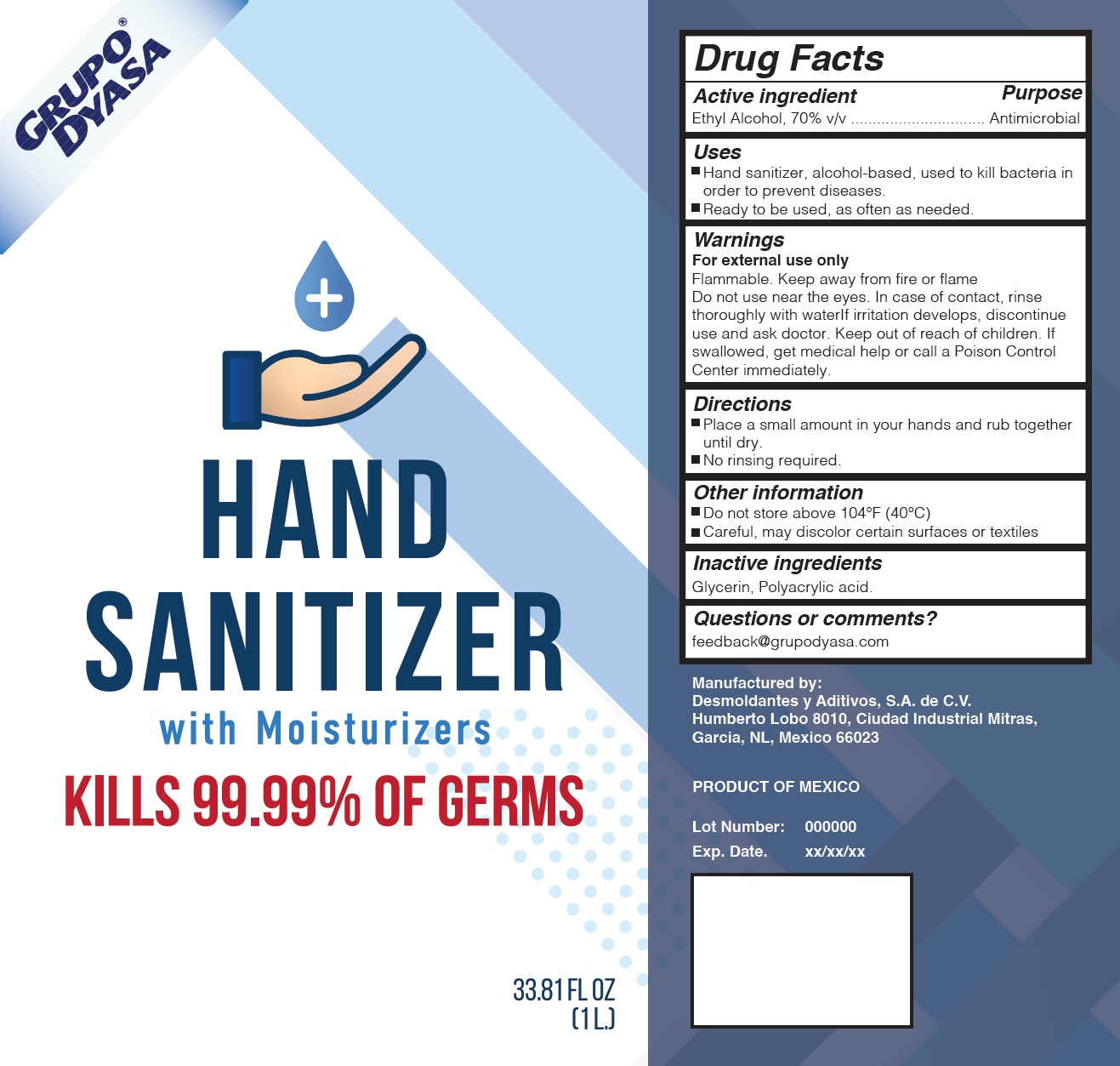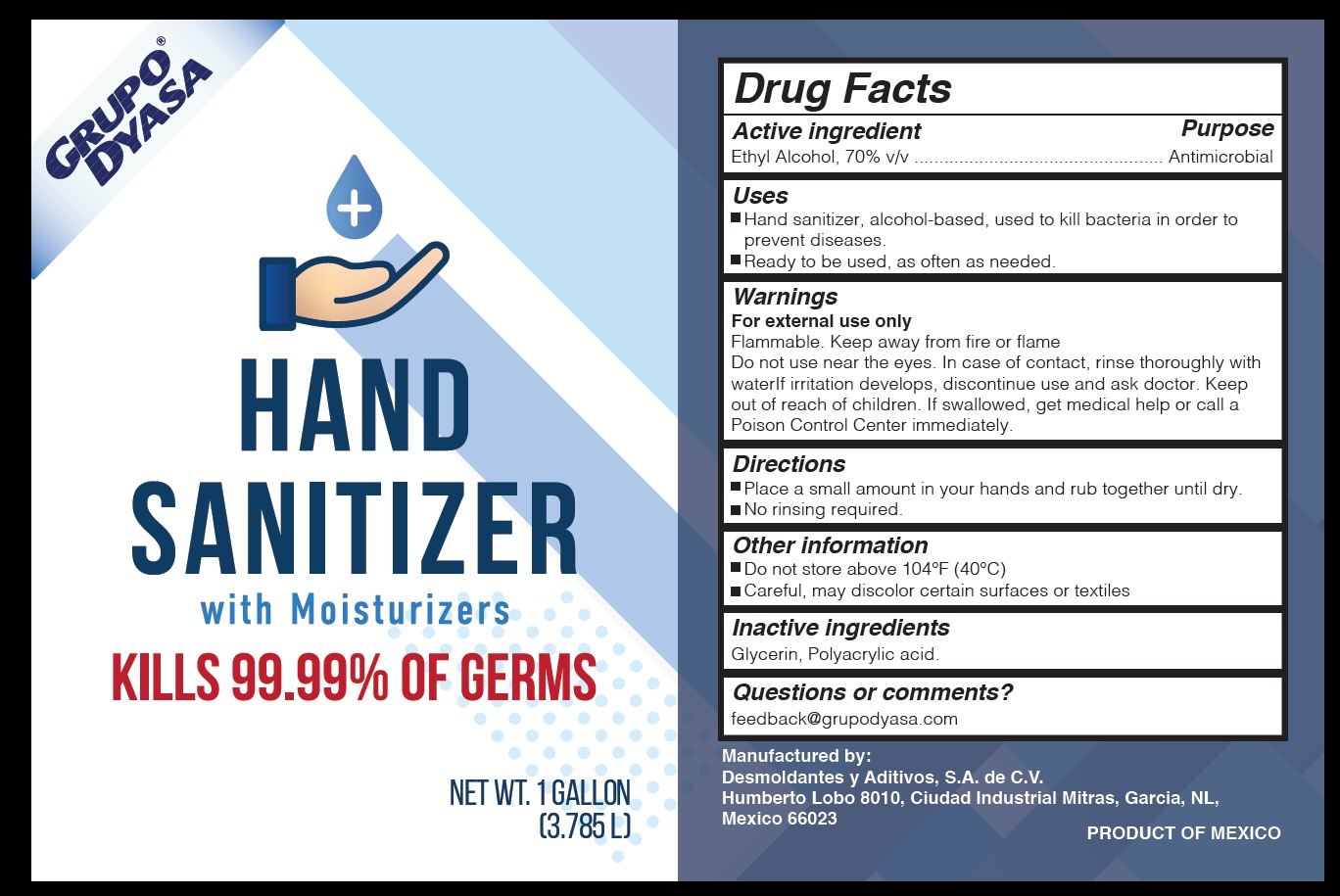 DRUG LABEL: Hand Sanitizer
NDC: 77357-000 | Form: GEL
Manufacturer: Desmoldantes y Aditivos, S.A. de C.V.
Category: otc | Type: HUMAN OTC DRUG LABEL
Date: 20200518

ACTIVE INGREDIENTS: ALCOHOL 0.7 L/1 L
INACTIVE INGREDIENTS: GLYCERIN

Hand Sanitizer

Active ingredient

Ethyl Alcohol, 70% v/v

Purpose

Antimicrobial

Uses

- Hand sanitizer, alcohol-based, used to kill bacteria in order to prevent diseases.

- Ready to be used, as often as needed.

Warnings

For external use only
Flammable. Keep away from fire or flame

Do not use

near the eyes. In case of contact, rinse thoroughly with waterIf irritation develops, discontinue use and ask doctor.

Keep out of reach of children.

If swallowed, get medical help or call a Poison Control Center immediately

Directions

- Place a small amount in your hands and rub together until dry.
- No rinsing required.

Inactive ingredients

Glycerin, Polyacrylic acid.

Questions or comments?

feedback@grupodyasa.com